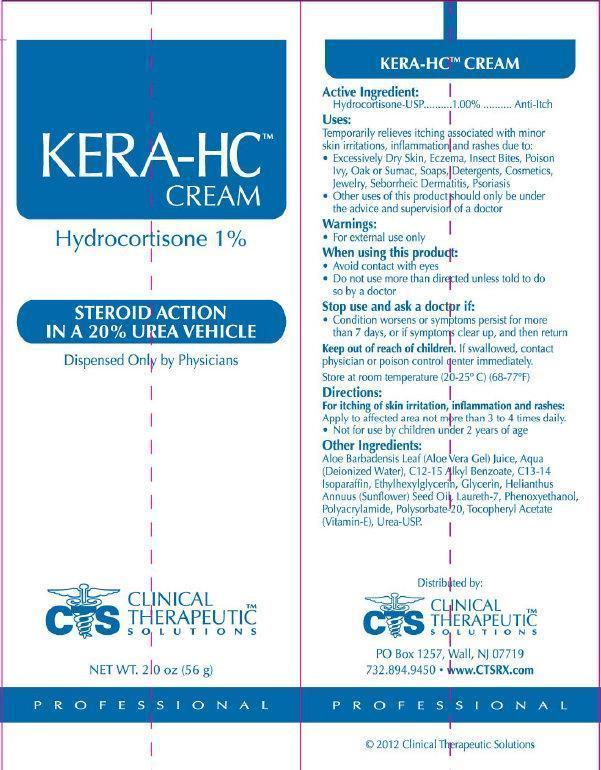 DRUG LABEL: KERA HC
NDC: 44577-623 | Form: CREAM
Manufacturer: Clinical Therapeutic Solutions
Category: otc | Type: HUMAN OTC DRUG LABEL
Date: 20231110

ACTIVE INGREDIENTS: HYDROCORTISONE 1 g/100 g
INACTIVE INGREDIENTS: ALOE VERA LEAF; WATER; ALKYL (C12-15) BENZOATE; C13-14 ISOPARAFFIN; ETHYLHEXYLGLYCERIN; GLYCERIN; SUNFLOWER OIL; LAURETH-7; PHENOXYETHANOL; POLYSORBATE 20; .ALPHA.-TOCOPHEROL; UREA

KERA HC Cream Hydrocortisone 1%

Active Ingredient

Hydrocortisone-USP 1.00%

Purpose

Anti-Itch

Uses:

Temporarily relieves itching associated with minor skin irritations, inflammations and rashes due to:

- Excessively Dry Skin, Eczema, Insect Bites, Poison Ivy, Oak or Sumac, Soaps, Detergents, Cosmetics, Jewelery, Seborrheic Dermatitis, Psoriasis
- Other uses of this product should only be under the advice and supervisor of a doctor

Warnings

- For external use only

When using this product:

- Avoid contact with eyes
- Do not use more than directed unless told to do so by a doctor

Stop use and ask a doctor if:

- Condition worsens or symptoms persist for more than 7 days, or if symptoms clear up, and then return

Keep out of reach of children.

If swallowed, contact physician or poison control center immediately.

Directions:

For itching of skin irritation, inflammation and rashes:

- Apply to affected area not more than 3 to 4 times daily.
- Not for use by children under 2 years of age

Other Ingredients:

Aloe Barbadensis Leaf (Aloe Vera Gel) Juice, Aqua (Deionized Water), C12-15 Alkyl Benzoate, c13-14 Isoparaffin, Ethylhexylglycerin, Glycerin, Heilianthus Annuus (Sunflower) Seed Oil, Laureth-7, Phenoxyethanol, Polacrylamide, Polysorbate-20, Tocopheryl Acetate (Vitamin E), Urea-USP.

Distributed By:

Clinical Therapeutic Solutions, PO Box 1257, Wall, NJ 07719 www.CTSRX.com